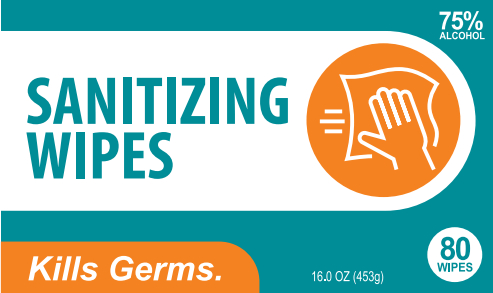 DRUG LABEL: Sanitizing wipes
NDC: 67984-003 | Form: CLOTH
Manufacturer: XIAMEN EASEPAL ENTERPRISES LIMITED
Category: otc | Type: HUMAN OTC DRUG LABEL
Date: 20200430

ACTIVE INGREDIENTS: ALCOHOL 291.18 mL/80 1
INACTIVE INGREDIENTS: WATER

DOSAGE AND ADMINISTRATION

Ergonomical packaging al lows for easy cary. Store in cool and dry place.

INACTIVE INGREDIENT

WATER

INDICATIONS AND USAGE

Peel back flap on front to pul out a towelette and wipe away. Reseal the flap to keep moisture sealed in.

ACTIVE INGREDIENT

ALCOHOL

keep out of reach of children

PURPOSE

Disinfection
Sterilization
No Rinseing

Keep out of reach of children. For extemal use only. Flammable, keep away from sources of fire or flame. Keep out of eyes. In case of eye contact, rinse eyes with water.Stop use and ask a doctor if redness or iritation develops.